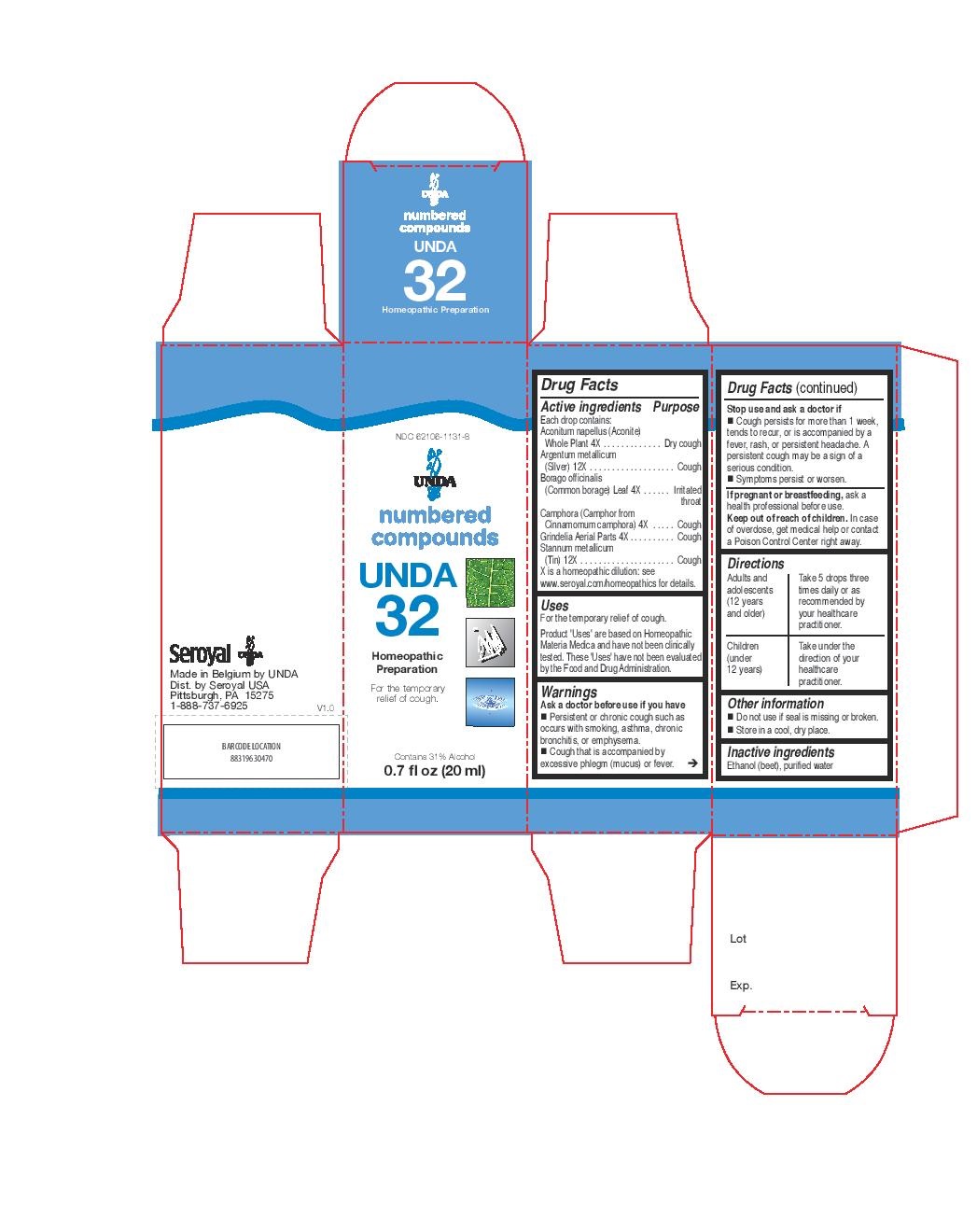 DRUG LABEL: UNDA 32
NDC: 62106-1131 | Form: LIQUID
Manufacturer: Seroyal USA
Category: homeopathic | Type: HUMAN OTC DRUG LABEL
Date: 20221109

ACTIVE INGREDIENTS: SILVER 12 [hp_X]/20 mL; TIN 12 [hp_X]/20 mL; ACONITUM NAPELLUS 4 [hp_X]/20 mL; BORAGE 4 [hp_X]/20 mL; GRINDELIA HIRSUTULA FLOWERING TOP 4 [hp_X]/20 mL; CAMPHOR (NATURAL) 4 [hp_X]/20 mL
INACTIVE INGREDIENTS: ALCOHOL; WATER

UNDA 32

Active ingredients
Each drop contains:
Aconitum napellus (Aconite) Whole Plant 4X
Argentum metallicum (Silver) 12X
Borago officinalis (Common borage) Leaf 4X
Camphora (Camphor from Cinnamomum camphora) 4X
Grindelia Aerial Parts 4X
Stannum metallicum (Tin) 12X

Uses
For the temporary relief of cough.

Warnings
Ask a doctor before use if you have
Persistent or chronic cough such as occurs with smoking, asthma, chronic bronchitis, or emphysema.
Cough that is accompanied by excessive phlegm (mucus) or fever.

Stop use and ask a doctor if

Cough persists for more than 1 week, tends to recur, or is accompanied by a fever, rash, or persistent headache. A
persistent cough may be a sign of a serious condition.
Symptoms persist or worsen.

If pregnant or breastfeeding, ask a health professional before use.
Keep out of reach of children. In case of overdose, get medical help or contact a Poison Control Center right away.

Ask a doctor before use if you have
Persistent or chronic cough such as occurs with smoking, asthma, chronic bronchitis, or emphysema.
Cough that is accompanied by excessive phlegm (mucus) or fever.

Stop use and ask a doctor if
Cough persists for more than 1 week, tends to recur, or is accompanied by a fever, rash, or persistent headache. A persistent cough may be a sign of a serious condition.

Symptoms persist or worsen.

PREGNANCY OR BREAST FEEDING

If pregnant or breastfeeding, ask a health professional before use.

Keep out of reach of children. In case of overdose, get medical help or contact a Poison Control Center right away.

Other information
Do not use if seal is missing or broken.
Store in a cool, dry place.

Inactive ingredients
Ethanol (beet), purified water

Directions
Adults and adolescents (12 years and older)

Take 5 drops three times daily or as recommended by your healthcare practitioner.
Children (under 12 years)

Take under the direction of your healthcare practitioner.

Uses
For the temporary relief of cough.

Directions

Adults and adolescents (12 years and older)

Take 5 drops three times daily or as recommended by your healthcare practitioner.

Children (under 12 years)

Take under the direction of your healthcare practitioner.

PACKAGE LABEL

NDC 62106-1131-8

UNDA

numbered compounds

UNDA 32

Homeopathic Preparation

For the temporary relief of cough.

Contains 31% Alcohol

0.7 fl oz (20 ml)